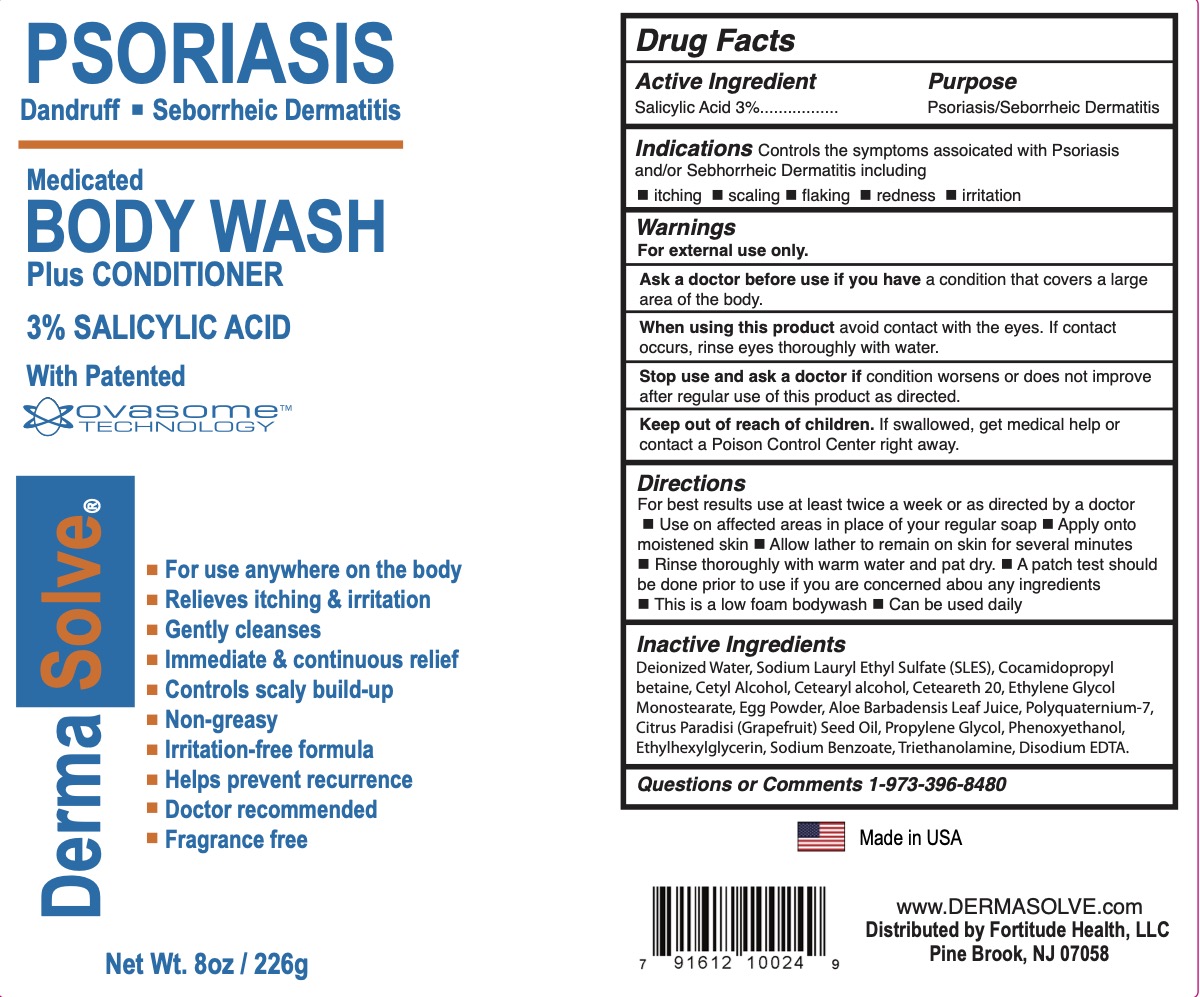 DRUG LABEL: DermaSolve Medicated
NDC: 84285-102 | Form: SOAP
Manufacturer: Fortitude Health, LLC
Category: otc | Type: HUMAN OTC DRUG LABEL
Date: 20241024

ACTIVE INGREDIENTS: SALICYLIC ACID 3 g/100 g
INACTIVE INGREDIENTS: CETEARETH-20; ETHYLHEXYLGLYCERIN; DIETHYLENE GLYCOL MONOSTEARATE; EGG; ALOE BARBADENSIS LEAF JUICE; CETYL ALCOHOL; COCAMIDOPROPYL BETAINE; GRAPEFRUIT SEED OIL; SODIUM LAURETH SULFATE; WATER; POLYQUATERNIUM-7; PHENOXYETHANOL; CETEARYL ALCOHOL; PROPYLENE GLYCOL; SODIUM BENZOATE; TROLAMINE; EDETATE DISODIUM

DermaSolve Body Wash

ACTIVE INGREDIENT

Salicylic Acid 3%

PURPOSE

Psoriasis/Seborrheic Dermatitis/Dandruff

INDICATIONS AND USAGE

Controls the symptoms associated with Psoriasis, Seborrheic Dermatitis and/or Dandruff including itching, scaling, flaking, redness, and irritation.

WARNINGS

For external use only.

Ask a doctor before use if you have a condition that covers a large are of the body.

When using this product avoid contact with the eyes. If contact occurs, rinse eyes thoroughly with water.

Stop use and ask a doctor if condition worsens or does not improve after regular use of this product as directed.

KEEP OUT OF REACH OF CHILDREN

If swallowed, get medical help or contact a Poison Control Center right away.

DOSAGE AND ADMINISTRATION

For best results use at least twice a week or as directed by a doctor.

- Use on affected areas in place of your regular soap
- Apply onto moistened skin
- Allow later to remain on skin for several minutes
- Rinse thoroughly with warm water and pat dry. For best results use at least twice a week or as directed by a doctor.
- A patch test should be done prior to use if you are concerned about any ingredients.
- This is a low foam shampoo.
- Can be used daily

INACTIVE INGREDIENT

Deionized Water, Sodium Laryl Ether Sulfate, Coamidopropyl Betaine, Cetyl Alcohol, Cetearyl Alcohol, Ceteareth-20, Ethylene Glycol Monostearate, Egg Powder, Aloe Barbadensis Leaf Juice, Polyquaternium-7, Citrus Paradisi (Grapefruit) Seed Oil, Propylene Glycol, Phenoxyethanol, Ethylhexylglycerin, Sodium Benzoate, Triethanolamine, Disodium EDTA.